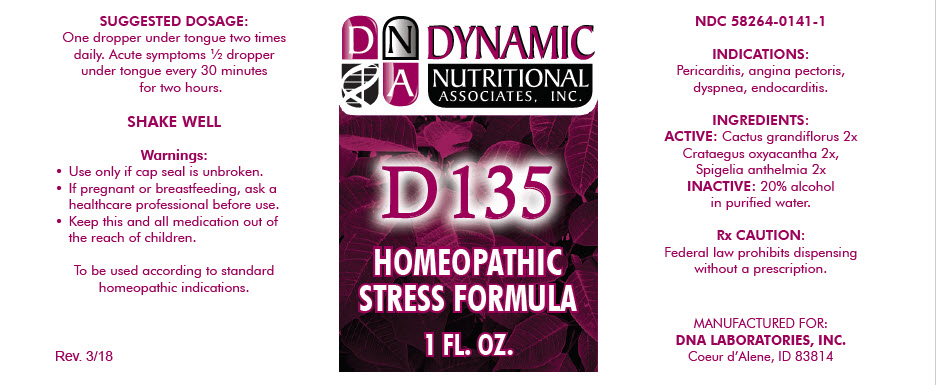 DRUG LABEL: D-135
NDC: 58264-0141 | Form: SOLUTION
Manufacturer: DNA Labs, Inc.
Category: homeopathic | Type: HUMAN OTC DRUG LABEL
Date: 20250113

ACTIVE INGREDIENTS: SELENICEREUS GRANDIFLORUS STEM 2 [hp_X]/1 mL; CRATAEGUS LAEVIGATA FRUIT 2 [hp_X]/1 mL; SPIGELIA ANTHELMIA 2 [hp_X]/1 mL
INACTIVE INGREDIENTS: ALCOHOL; WATER

D-135

NDC 58264-0141-1

INDICATIONS

PURPOSE

Pericarditis, angina pectoris, dyspnea, endocarditis.

INGREDIENTS

ACTIVE

Cactus grandiflorus 2x Crataegus oxyacantha 2x, Spigelia anthelmia 2x

INACTIVE

20% alcohol in purified water.

Rx CAUTION

Federal law prohibits dispensing without a prescription.

SUGGESTED DOSAGE

One dropper under tongue two times daily. Acute symptoms ½ dropper under tongue every 30 minutes for two hours.

STORAGE AND HANDLING

SHAKE WELL

Warnings

- Use only if cap seal is unbroken.

PREGNANCY OR BREAST FEEDING

- If pregnant or breastfeeding, ask a healthcare professional before use.

KEEP OUT OF REACH OF CHILDREN

- Keep this and all medication out of the reach of children.

To be used according to standard homeopathic indications.

PRINCIPAL DISPLAY PANEL - 1 FL. OZ. Bottle Label

DYNAMIC
NUTRITIONAL
ASSOCIATES, INC.

D 135

HOMEOPATHIC
STRESS FORMULA

1 FL. OZ.